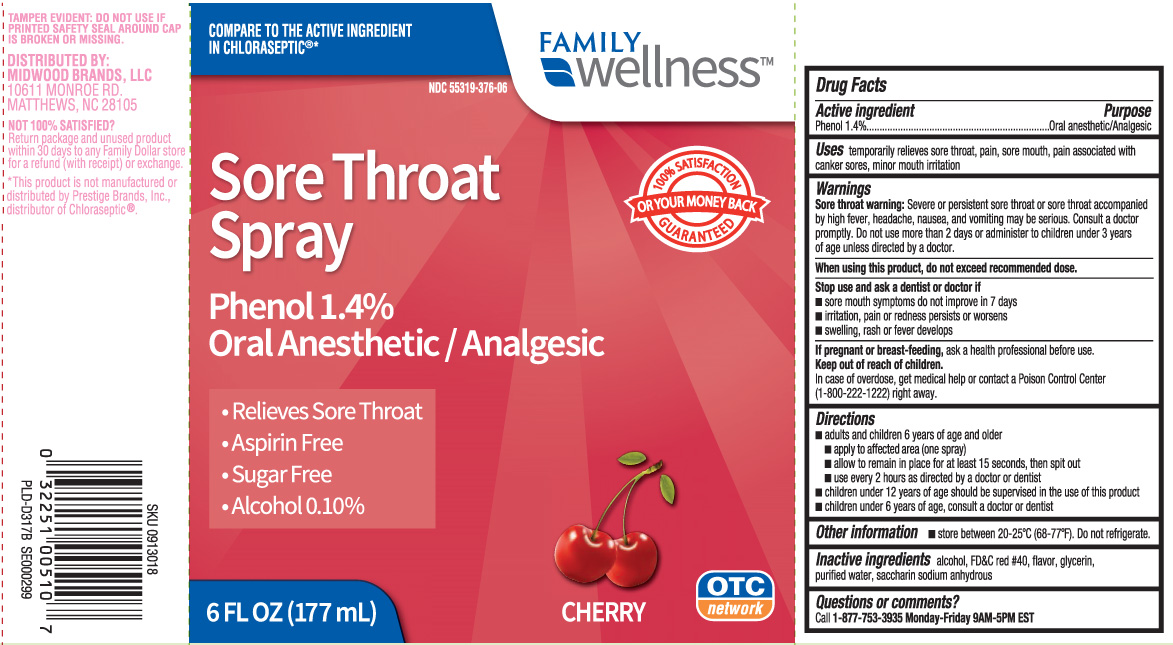 DRUG LABEL: Sore Throat
NDC: 55319-376 | Form: SPRAY
Manufacturer: Family Dollar (FAMILY WELLNESS)
Category: otc | Type: HUMAN OTC DRUG LABEL
Date: 20240327

ACTIVE INGREDIENTS: PHENOL 1.4 g/100 mL
INACTIVE INGREDIENTS: ALCOHOL; FD&C RED NO. 40; GLYCERIN; WATER; SACCHARIN SODIUM

Drug Facts

Active ingredient

Phenol 1.4%

Purpose

Oral Anesthetic/Analgesic

Uses

temporarily relieves sore throat pain, sore mouth, pain associated with canker sores, minor mouth irritation

Warnings

Sore throat warning: Severe or persistent sore throat or sore throat that occurs with high fever, headache, nausea, and vomiting may be serious. Consult a doctor promptly. Do not use more than 2 days or administer to children under 3 years of age unless directed by a doctor.

When using this product,

do not exceed recommended dose.

Stop use and ask a dentist or doctor if

- swelling, rash or fever develops
- irritation, pain or redness persists or worsens
- sore mouth symptoms do not improve in 7 days

If pregnant or breast-feeding,

ask a health professional before use.

Keep out of reach of children.

In case of overdose, get medical help or contact a Poison Control Center (1-800-222-1222) right away.

Directions

- adults and children 6 years of age and older
  - apply to affected area (one spray)
  - allow to remain in place for at least 15 seconds, then spit out
  - use every 2 hours as directed by a doctor or dentist
- children under 12 years of age should be supervised in the use of this product
- children under 6 years of age, consult a doctor or dentist

Other information

- store between 20-25ºC (68-77ºF). Do not refrigerate.

Inactive ingredients

alcohol, FD&C red #40, glycerin, flavor, purified water, saccharin sodium

Questions or comments?

Call 1-877-753-3935 Monday-Friday 9AM-5PM EST

Principal Display Panel

COMPARE TO THE ACTIVE INGREDIENT IN CHLORASEPTIC®*

Sore Throat Spray

Phenol/Oral Anesthetic

- Relieves Sore Throat
- Aspirin Free
- Sugar Free
- Alcohol 0.10%

CHERRY

FL OZ (mL)

*This product is not manufactured or distributed by Prestige Brands, Inc., distributor of Chloraseptic®.

TAMPER EVIDENT: DO NOT USE IF PRINTED SAFETY SEAL AROUND CAP IS BROKEN OR MISSING

DISTRIBUTED BY:

MIDWOOD BRANDS, LLC

10611 MONROE RD,

MATTHEWS, NC 28105

Package Label

FAMILY WELLNESS Sore throat Spray Cherry Flavor